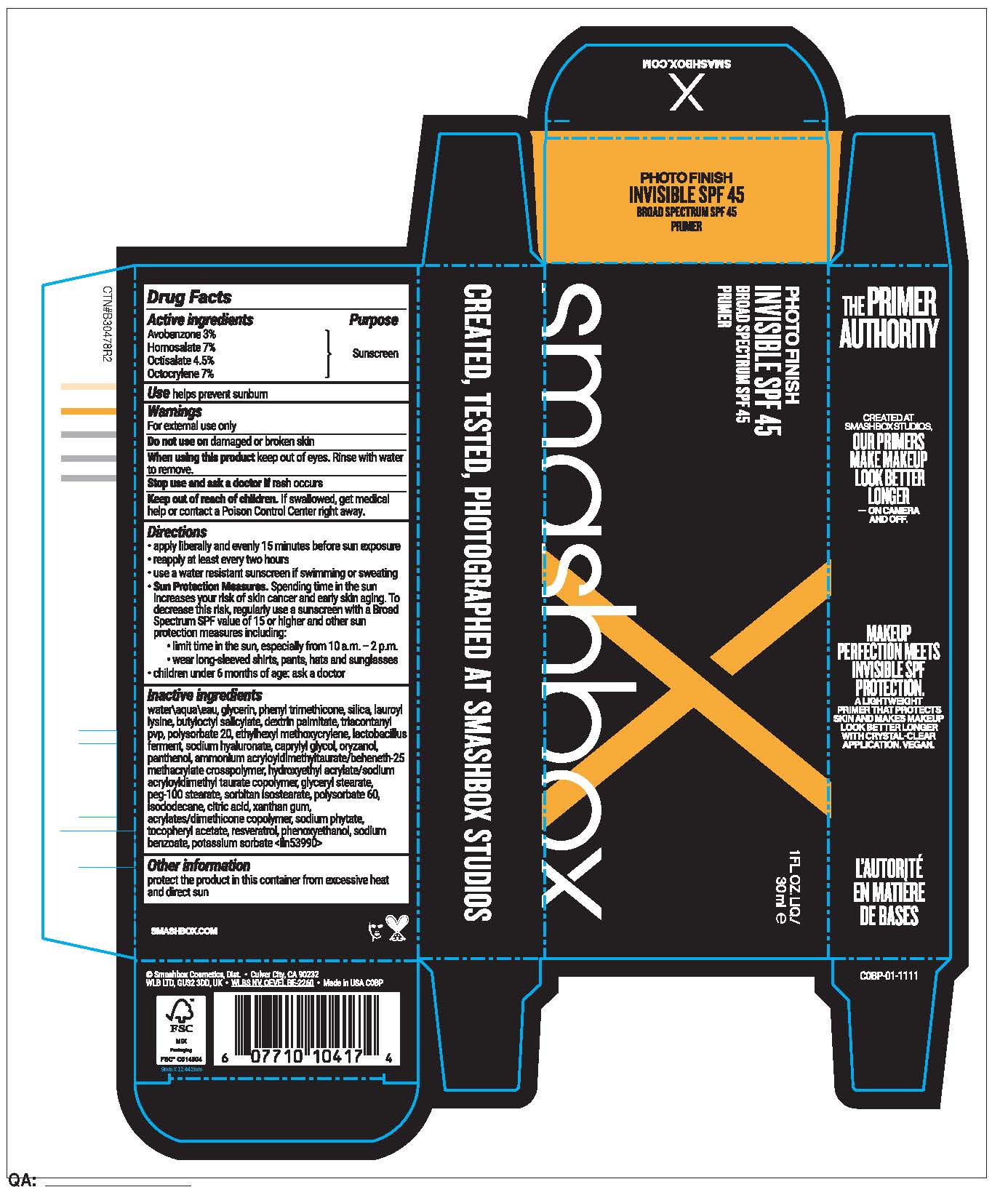 DRUG LABEL: PHOTO FINISH INVISIBLE SPF 45 BROAD SPECTRUM SPF 45 PRIMER
NDC: 10348-019 | Form: LIQUID
Manufacturer: SMASHBOX BEAUTY COSMETICS, INC
Category: otc | Type: HUMAN OTC DRUG LABEL
Date: 20251022

ACTIVE INGREDIENTS: OCTISALATE 45 mg/1 mL; OCTOCRYLENE 70 mg/1 mL; HOMOSALATE 70 mg/1 mL; AVOBENZONE 30 mg/1 mL
INACTIVE INGREDIENTS: WATER; GLYCERIN; DEXTRIN PALMITATE (CORN; 20000 MW); POTASSIUM SORBATE; SODIUM BENZOATE; RESVERATROL; SILICA; TRIACONTANYL PVP; POLYSORBATE 20; PHENOXYETHANOL; LIMOSILACTOBACILLUS FERMENTUM; HYDROXYETHYL ACRYLATE/SODIUM ACRYLOYLDIMETHYL TAURATE COPOLYMER (45000 MPA.S AT 1%); LAUROYL LYSINE; CAPRYLYL GLYCOL; SORBITAN ISOSTEARATE; POLYSORBATE 60; BUTYLOCTYL SALICYLATE; ISODODECANE; ALPHA-TOCOPHEROL ACETATE; PHENYL TRIMETHICONE; ORYZANOL; CITRIC ACID; XANTHAN GUM; PANTHENOL; AMMONIUM ACRYLOYLDIMETHYLTAURATE/BEHENETH-25 METHACRYLATE CROSSPOLYMER (52000 MPA.S); GLYCERYL STEARATE; PEG-100 STEARATE; SODIUM HYALURONATE; ETHYLHEXYL METHOXYCRYLENE

PHOTO FINISH INVISIBLE SPF 45 BROAD SPECTRUM SPF 45 PRIMER

Active ingredients

Avobenzone 3%

Homosalate 7%

Octisalate 4.5%

Octocrylene 7%

Purpose

Sunscreen

Use

helps prevent sunburn

Warnings

For external use only

Do not use

on damaged or broken skin

When using this product

kepp out of eyes. Rinse with water to remove

Stop use and ask a doctor if

rash occurs

Keep out of reach of childeren

if swallowed, get medical help or contact a Poison Control Center right away.

Directions

apply liberally and evenly15 minutes before sun exposure
reapply at least every two hours
use a water resistant sunscreen if swimming or sweating
Sun Protection Measures. Spending time in the sun increases your risk of skin cancer and early skin aging. To decrease this risk, regularly use a sunscreen with a Broad Spectrum SPF value of 15 or higher and other sun protection measures including:
limit time in the sun, especially from 10 a.m.–2 p.m.
wear long-sleeved shirts, pants, hats and sunglasses

children under 6 months of age: ask a doctor

Inactive ingredients

water\aqua\eau , glycerin , phenyl trimethicone , silica , lauroyl lysine , butyloctyl salicylate , dextrin palmitate , triacontanyl pvp , polysorbate 20 , ethylhexyl methoxycrylene , lactobacillus ferment , sodium hyaluronate , caprylyl glycol , oryzanol , panthenol , ammonium acryloyldimethyltaurate/beheneth-25 methacrylate crosspolymer , hydroxyethyl acrylate/sodium acryloyldimethyl taurate copolymer , glyceryl stearate , peg-100 stearate , sorbitan isostearate , polysorbate 60 , isododecane , citric acid , xanthan gum , acrylates/dimethicone copolymer , sodium phytate , tocopheryl acetate , resveratrol , phenoxyethanol , sodium benzoate , potassium sorbate <iln53990>

Other information

protect the product in this container from excessive heat and direct sun

PDP

PHOTO FINISH INVISIBLE SPF 45

BROAD SPECTRUM SPF 45

PRIMER

SMASHBOX

1FL OZ LIQ/30ML